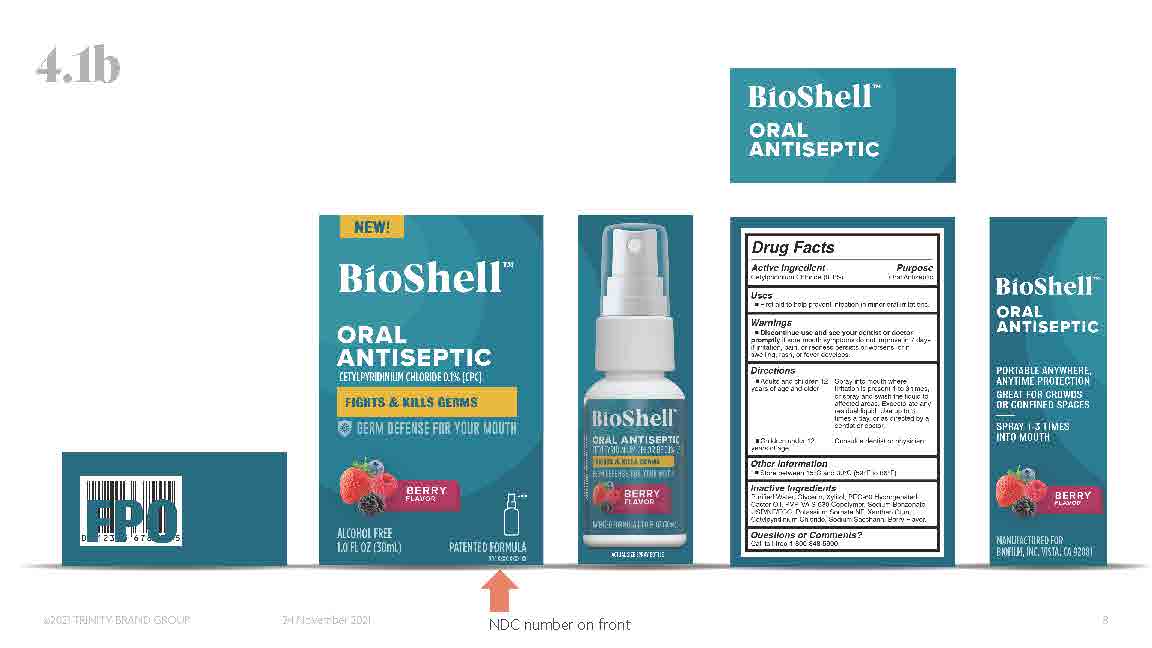 DRUG LABEL: BioShell
NDC: 66357-120 | Form: SPRAY
Manufacturer: BioFilm, Inc.
Category: otc | Type: HUMAN OTC DRUG LABEL
Date: 20220317

ACTIVE INGREDIENTS: CETYLPYRIDINIUM CHLORIDE 0.1 g/100 mL
INACTIVE INGREDIENTS: POTASSIUM SORBATE; WATER; XANTHAN GUM; XYLITOL; PEG-60 HYDROGENATED CASTOR OIL; SODIUM BENZOATE; GLYCERIN; SACCHARIN SODIUM

BioShell

Active ingredients

Cetylpridinium Chloride 0.1% -- Oral Antiseptic

Purpose

Oral Antiseptic

Uses

First aid to help prevent infection in minor oral irritations

Warnings

- Discontinue use and see your dentist or doctor promptly if sore mouth symptoms do not improve in 7 days, if irritation pain, or redness persists or worsens, or if swelling, rash, or fever develops.
- Do not use children under 12 years of age
- Keep out of reach of children
- If more than used for rinsing is accidentally swallowed, get medical help or contact a Poison Control Center right away.

Directions

- Adults and children 12 years of age and older: spray into mouth where irritation is present 1 to 3 times, or spray and swish the liquid to affected areas. Expectorate any residual liquid. Use up to 3 times a day, or as directed by a dentist or doctor.
- Children under 12 years of age: consult a dentist or physician.

KEEP OUT OF REACH OF CHILDREN UNDER 6 YEARS OF AGE.

If more than used for rinsing is accidentally swallowed, get medical help or contact a Poison Contol Center right away.

Other Information

Store between 15C and 30C (59F to 86F)

Inactive ingredients

Purified water, Glycerin, Xylitol, PEG-60 Hydrogenated Castor Oil, PVP-VA S-630 Copolymer, Sodium Benzonate USP/NF/FCC, Potassium Sorbate NF, Xanthan Gum, Sodium Saccharin, Berry Flavor.

Questions or Comments?

Call toll-free 1-800-848-5900